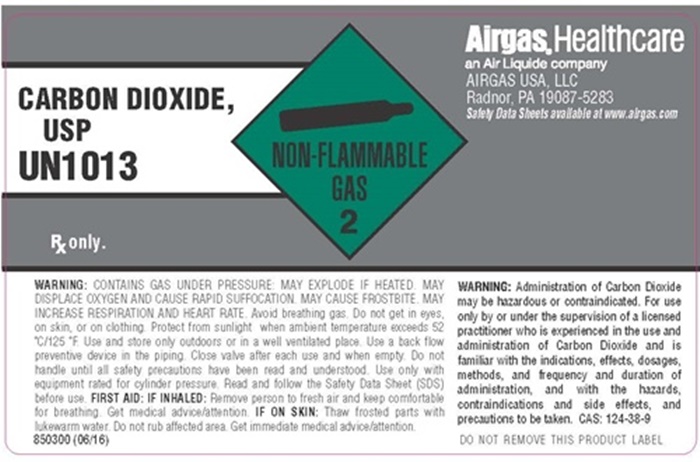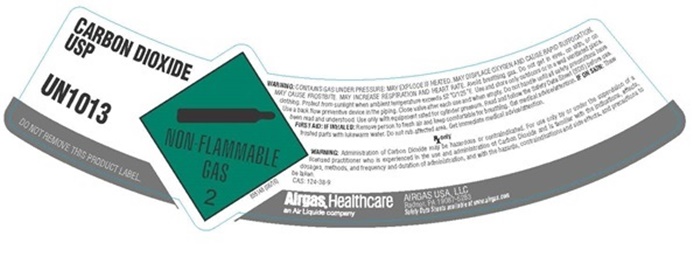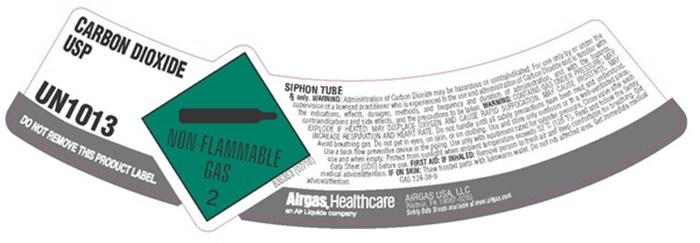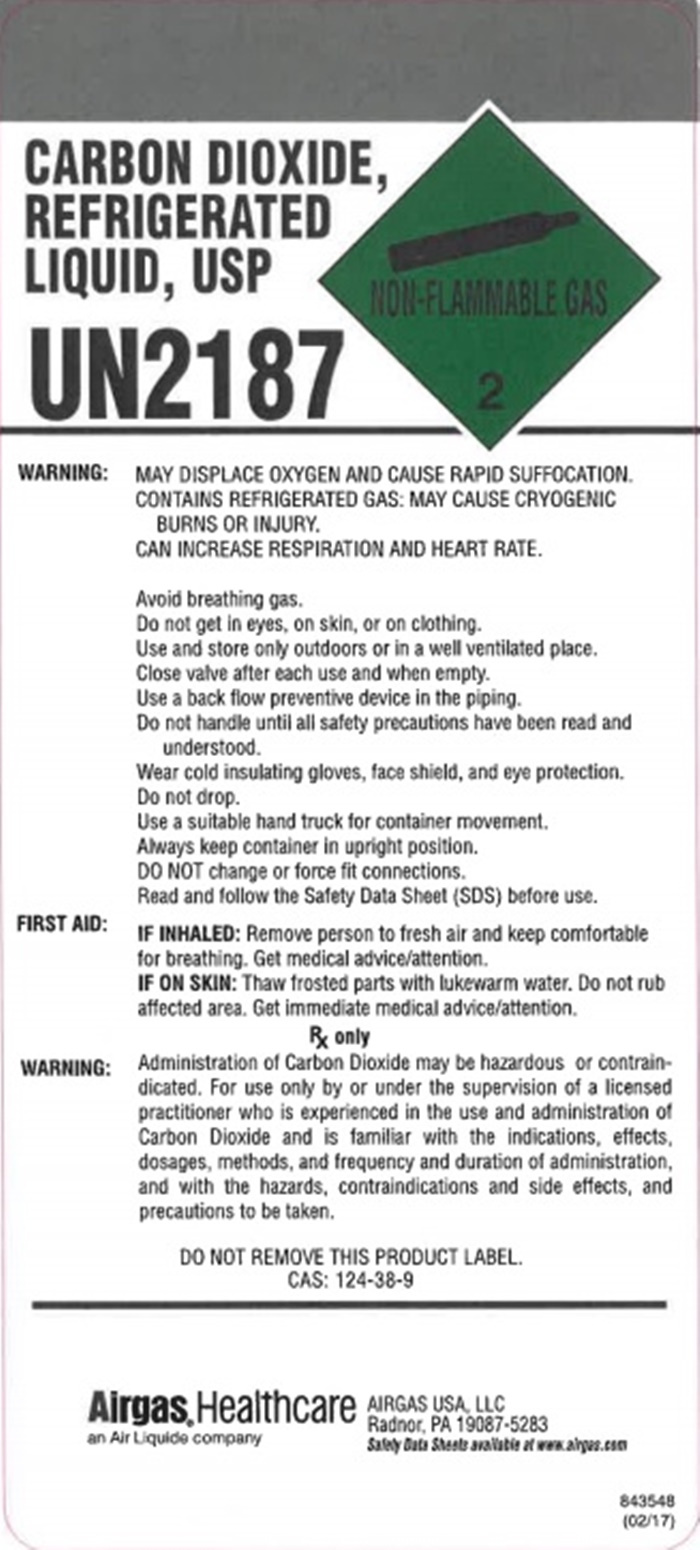 DRUG LABEL: Carbon Dioxide
NDC: 11054-130 | Form: GAS
Manufacturer: Airgas Usa, LLC
Category: prescription | Type: HUMAN PRESCRIPTION DRUG LABEL
Date: 20241001

ACTIVE INGREDIENTS: Carbon Dioxide 992 mL/1 L

Carbon Dioxide 130

Airgas CO2 Shoulder label

CARBON DIOXIDE USP UN1013

DO NOT REMOVE THIS PRODUCT LABEL

NON-FLAMMABLE GAS 2

Airgas, Healthcare an Air Liquide company

AIRGAS USA LLC

Radnor, PA 19087-5283

Safety Data Sheets available at www.airgas.com

WARNING: CONTAINS GAS UNDER PRESSURE. MAY EXPLODE IF HEATED. MAY DISPLACE OXYGEN AND CAUSE RAPID SUFFOCATION. MAY CAUSE FROSTBITE. MAY INCREASE RESPIRATION AND HEART RATE. Avoid breathing gas. Do not get in eyes or skin or on clothing. Protect from sunlight when ambient temperature exceeds 52°C (125°F). Use and store only outdoors or in a well-ventilated place. Use a back-flow preventive device in the piping. Close valve after each use and when empty. Do not handle until all safety precautions have been read and understood. Use only with equipment rated for cylinder pressure. Read and follow the Safety Data Sheet (SDS) before use. FIRST AID: IF INHALED: Remove person to fresh air and keep comfortable for breathing. Get medical advice/attention. IF ON SKIN: Thaw frosted parts with lukewarm water. Do not rub affected area. Get immediate medical advice/attention.

Rx only.

WARNING: Administration of Carbon Dioxide may be hazardous or contraindicated. For use only by or under the supervision of a licensed practioner who is experienced in the use and administration of Carbon Dioxide and is familiar with the indications, effects, dosages, methods, and frequency and duration of administration, and with the hazards contraindications and side effects and precautions to be taken.

CAS: 124-38-9

Airgas CO2 Body Label

CARBON DIOXIDE USP UN1013

Rx only.

NON-FLAMMABLE GAS 2

Airgas, Healthcare an Air Liquide company

AIRGAS USA LLC

Radnor, PA 19087-5283

Safety Data Sheets available at www.airgas.com

WARNING: CONTAINS GAS UNDER PRESSURE. MAY EXPLODE IF HEATED. MAY DISPLACE OXYGEN AND CAUSE RAPID SUFFOCATION. MAY CAUSE FROSTBITE. MAY INCREASE RESPIRATION AND HEART RATE. Avoid breathing gas. Do not get in eyes or skin or on clothing. Protect from sunlight when ambient temperature exceeds 52°C (125°F). Use and store only outdoors or in a well-ventilated place. Use a back-flow preventive device in the piping. Close valve after each use and when empty. Do not handle until all safety precautions have been read and understood. Use only with equipment rated for cylinder pressure. Read and follow the Safety Data Sheet (SDS) before use. FIRST AID: IF INHALED: Remove person to fresh air and keep comfortable for breathing. Get medical advice/attention. IF ON SKIN: Thaw frosted parts with lukewarm water. Do not rub affected area. Get immediate medical advice/attention.

850300 (06/16)

WARNING: Administration of Carbon Dioxide may be hazardous or contraindicated. For use only by or under the supervision of a licensed practioner who is experienced in the use and administration of Carbon Dioxide and is familiar with the indications, effects, dosages, methods, and frequency and duration of administration, and with the hazards contraindications and side effects and precautions to be taken.

CAS: 124-38-9

DO NOT REMOVE THIS PRODUCT LABEL

Airgas CO2 Siphon

CARBON DIOXIDE USP UN1013

DO NOT REMOVE THIS PRODUCT LABEL

NON-FLAMMABLE GAS 2

SIPHON TUBE

Rx only. WARNING: Administration of Carbon Dioxide may be hazardous or contraindicated. For use only by or under the supervision of a licensed practioner who is experienced in the use and administration of Carbon Dioxide and is familiar with the indications, effects, dosages, methods, and frequency and duration of administration, and with the hazards contraindications and side effects and precautions to be taken. WARNING: CONTAINS GAS UNDER PRESSURE. MAY EXPLODE IF HEATED. MAY DISPLACE OXYGEN AND CAUSE RAPID SUFFOCATION. MAY CAUSE FROSTBITE. MAY INCREASE RESPIRATION AND HEART RATE. Avoid breathing gas. Do not get in eyes or skin or on clothing. Protect from sunlight when ambient temperature exceeds 52°C (125°F). Use and store only outdoors or in a well-ventilated place. Use a back-flow preventive device in the piping. Close valve after each use and when empty. Do not handle until all safety precautions have been read and understood. Use only with equipment rated for cylinder pressure. Read and follow the Safety Data Sheet (SDS) before use. FIRST AID: IF INHALED: Remove person to fresh air and keep comfortable for breathing. Get medical advice/attention. IF ON SKIN: Thaw frosted parts with lukewarm water. Do not rub affected area. Get immediate medical advice/attention.

CAS: 124-38-9

Airgas, Healthcare an Air Liquide company

AIRGAS USA LLC

Radnor, PA 19087-5283

Safety Data Sheets available at www.airgas.com

Airgas Refrigerated CO2

CARBON DIOXIDE, REFRIGERATED LIQUID, USP UN2187

NON-FLAMMABLE GAS 2

WARNING: MAY DISPLACE OXYGEN AND CAUSE RAPID SUFFOCATION. CONTAINS REFRIGERATED GAS. MAY CAUSE CRYOGENIC BURNS OR INJURY. CAN INCREASE RESPIRATION AND HEART RATE.

Avoid breathing gas. Do not get in eyes or skin or on clothing. Use and store only outdoors or in a well-ventilated place. Close valve after each use and when empty. Use a back-flow preventive device in the piping. Do not handle until all safety precautions have been read and understood. Wear cold insulating gloves, face shield, and eye protection. Do not drop. Use a suitable hand truck for container movement. Always keep container in upright position. DO NOT change or force fit connections. Read and follow the Safety Data Sheet (SDS) before use.

FIRST AID: IF INHALED: Remove person to fresh air and keep comfortable for breathing. Get medical advice/attention. IF ON SKIN: Thaw frosted parts with lukewarm water. Do not rub affected area. Get immediate medical advice/attention.

Rx only.

WARNING: Administration of Carbon Dioxide may be hazardous or contraindicated. For use only by or under the supervision of a licensed practioner who is experienced in the use and administration of Carbon Dioxide and is familiar with the indications, effects, dosages, methods, and frequency and duration of administration, and with the hazards contraindications and side effects and precautions to be taken.

DO NOT REMOVE THIS PRODUCT LABEL

CAS: 124-38-9

Airgas, Healthcare an Air Liquide company

AIRGAS USA LLC

Radnor, PA 19087-5283

Safety Data Sheets available at www.airgas.com